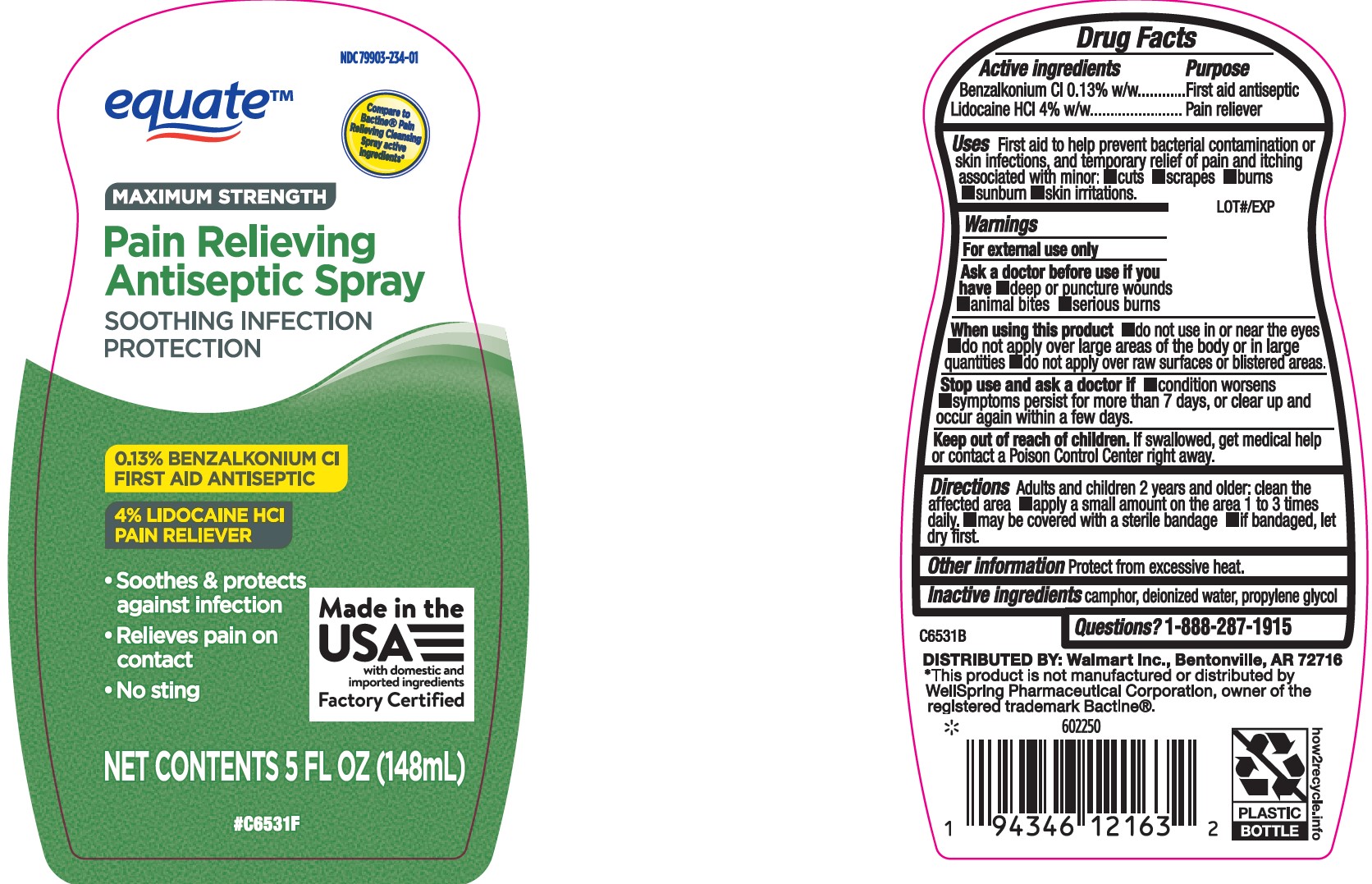 DRUG LABEL: Pain Relieving Antiseptic
NDC: 79903-234 | Form: SPRAY
Manufacturer: Walmart, Inc.
Category: otc | Type: HUMAN OTC DRUG LABEL
Date: 20240617

ACTIVE INGREDIENTS: BENZALKONIUM CHLORIDE 0.13 g/100 mL; LIDOCAINE HYDROCHLORIDE 4 g/100 mL
INACTIVE INGREDIENTS: WATER; CAMPHOR, (-)-; PROPYLENE GLYCOL

Equate Maximum Strength Pain Relieving Antiseptic Spray

Drug Facts

Active ingredients | Purpose
Benzalkonium CI 0.13% w/w | First aid antiseptic
Lidocaine HCI 4% w/w | Pain reliever

INACTIVE INGREDIENT

Uses First aid to help prevent bacterial contamination or skin infections, and temporary relief of pain and itching associated with minor: ■cuts ■scrapes ■burns ■sunburn ■skin irritations.

Uses

First aid to help prevent bacterial contamination or skin infections and temporary relief of pain and itching associated with:

■cuts ■scrapes ■burns ■sunburn ■skin irritations

Warnings

OTHER SAFETY INFORMATION

For external use only

Ask a doctor before use if you have ■deep or puncture wounds ■animal bites ■serious burns

When using this product ■do not use in or near the eyes ■do not apply over large areas of the body or in large quantities ■do not apply over raw surfaces or blistered areas.

Stop use and ask a doctor if ■condition worsens ■symptoms persist for more than 7 days, or clear up and occur again within a few days.

Keep out of reach of children. If swallowed, get medical help or contact a Poison Control Center right away.

DOSAGE AND ADMINISTRATION

Drections Adults and children 2 years and older: clean the affected area ■apply a small amount on the area 1 to 3 times daily. ■may be covered with a sterile bandage ■if bandaged, let dry first.

Other information Protect from excessive heat.

Inactive ingredients Camphor, Deionized water, Propylene glycol

Questions? 1-888-287-1915

PURPOSE

First aid to help prevent bacterial contamination or skin infections, and temporary relief of pain and itching associated with minor: ■cuts ■scrapes ■burns ■sunburn ■skin irritations.

PACKAGE LABEL

NDC# 79903-234-01

5 FL OZ (148 mL)